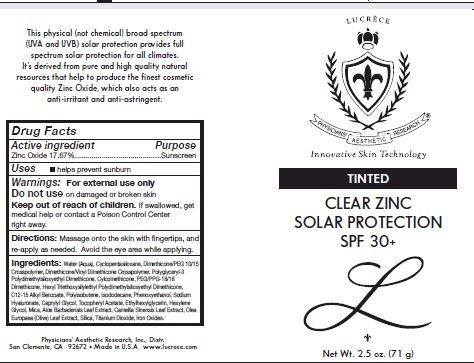 DRUG LABEL: Tinted Clear Zinc Solar Protection SPF 30
NDC: 62742-4112 | Form: CREAM
Manufacturer: Allure Labs, Inc
Category: otc | Type: HUMAN OTC DRUG LABEL
Date: 20171204

ACTIVE INGREDIENTS: ZINC OXIDE 176.7 mg/1 g
INACTIVE INGREDIENTS: WATER; CYCLOMETHICONE 5; DIMETHICONE/VINYL DIMETHICONE CROSSPOLYMER (SOFT PARTICLE); POLYGLYCERYL-3 POLYDIMETHYLSILOXYETHYL DIMETHICONE (4000 MPA.S); CYCLOMETHICONE; PEG/PPG-18/18 DIMETHICONE; ALKYL (C12-15) BENZOATE; POLYISOBUTYLENE (1000 MW); ISODODECANE; PHENOXYETHANOL; HYALURONATE SODIUM; CAPRYLYL GLYCOL; .ALPHA.-TOCOPHEROL ACETATE; ETHYLHEXYLGLYCERIN; HEXYLENE GLYCOL; MICA; ALOE; CAMELLIA SINENSIS FLOWER; OLEA EUROPAEA LEAF; TITANIUM DIOXIDE; FERRIC OXIDE RED; FERRIC OXIDE YELLOW; FERROSOFERRIC OXIDE

Drug Facts

ACTIVE INGREDIENT

Zinc Oxide 17.67%

DOSAGE AND ADMINISTRATION

Directions: Masasge onto skin with fingertips, and reapply as needed. Avoid eye area while applying.

For external use only.

INACTIVE INGREDIENT

Other Ingredients: Water (Aqua), Cyclopentasiloxane, Dimethcone/PEG-10/15 Crosspolymer, Dimethicone/Vinyl Dimethicone Crossploymer, Polyglyceryl-3 polydimethylsiloxyethyl Dimethicone, Cyclomethicone, PEG/PPG-18/18 Dimethicone, Hexyl triethoxysilylethyl Polydimethylsiloxyethyl Dimethicone, C12-15 Alkul benzoate, Poluisobutene, Isododecane, Phenoxyethanol, Sodium Hyaluronate, Caprylyl Glycol, Tocopheryl Acetate, Ethylhexylglycerin, Hexylene Glycol, Mica, Aloe barbadensis Leaf extract, Camellia Sinensis Leaf extract, Olea Europaea (Olive) Leaf Extarct, Silica, Titanium Dioxide, Iron Oxides

PACKAGE LABEL

Physicians Aesthetic

Research, Inc.

www.lucrece.com